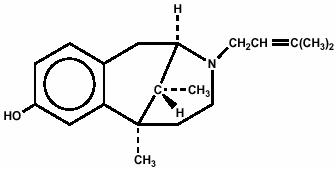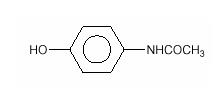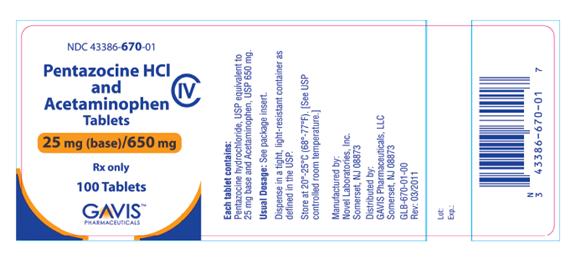 DRUG LABEL: Pentazocine Hydrochloride and Acetaminophen
NDC: 43386-670 | Form: TABLET
Manufacturer: GAVIS Pharmaceuticals, LLC
Category: prescription | Type: HUMAN PRESCRIPTION DRUG LABEL
Date: 20110712
DEA Schedule: CIV

ACTIVE INGREDIENTS: PENTAZOCINE HYDROCHLORIDE 25 mg/1 1; ACETAMINOPHEN 650 mg/1 1
INACTIVE INGREDIENTS: SILICON DIOXIDE; FD&C BLUE NO. 1; CELLULOSE, MICROCRYSTALLINE; SODIUM LAURYL SULFATE; SODIUM STARCH GLYCOLATE TYPE A POTATO; STEARIC ACID

Pentazocine Hydrochloride and Acetaminophen Tablets

Hepatotoxicity

Pentazocine Hydrochloride and Acetaminophen Tablets contain acetaminophen and pentazocine hydrochloride. Acetaminophen has been associated with cases of acute liver failure, at times resulting in liver transplant and death. Most of the cases of liver injury are associated with the use of acetaminophen at doses that exceed 4000 milligrams per day, and often involve more than one acetaminophen-containing product.

DESCRIPTION

Pentazocine Hydrochloride and Acetaminophen Tablets are a combination of pentazocine hydrochloride, USP, equivalent to 25 mg base and acetaminophen, USP, 650 mg.

Pentazocine is a member of the benzazocine series (also known as the benzomorphan series). Chemically, pentazocine is (2R*,6R*,11R*)1,2,3,4,5,6-hexahydro-6,11-dimethyl-3-(3-methyl-2-butenyl)-2,6-methano-3-benzazocin-8-ol, a white, crystalline substance soluble in acidic aqueous solutions, and has the following structural formula:

C19H27NO HCl M.W. 321.88

Chemically, acetaminophen is Acetamide, N-(4-hydroxyphenyl)-, and has the following structural formula:

C8H9NO2 M.W. 151.16

Pentazocine is an analgesic and acetaminophen is an analgesic and antipyretic.

Inactive ingredients: colloidal silicon dioxide, FD&C Blue # 1 aluminum lake, microcrystalline cellulose, sodium lauryl sulfate, sodium starch glycolate, and stearic acid.

CLINICAL PHARMACOLOGY

Pentazocine is a Schedule IV opioid analgesic with agonist/antagonist action which when administered orally is approximately equivalent on a mg for mg basis in analgesic effect to codeine.

Acetaminophen is an analgesic and antipyretic.

Pentazocine weakly antagonizes the analgesic effects of morphine, meperidine, and phenazocine; in addition, it produces incomplete reversal of cardiovascular, respiratory, and behavioral depression induced by morphine and meperidine. Pentazocine has about 1/50 the antagonistic activity of nalorphine. It also has sedative activity.

Onset of significant analgesia with pentazocine usually occurs between 15 and 30 minutes after oral administration, and duration of action is usually three hours or longer.

Pentazocine is well absorbed from the gastrointestinal tract. Plasma levels closely correspond to the onset, duration, and intensity of analgesia. The time to mean peak concentration in 24 normal volunteers was 1.7 hours (range 0.5 to 4 hours) after oral administration and the mean plasma elimination half-life was 3.6 hours (range 1.5 to 10 hours).

The action of pentazocine is terminated for the most part by biotransformation in the liver with some free pentazocine excreted in the urine. The products of the oxidation of the terminal methyl groups and glucuronide conjugates are excreted by the kidney. Elimination of approximately 60% of the total dose occurs within 24 hours. Pentazocine passes into fetal circulation.

Onset of significant analgesic and antipyretic activity of acetaminophen when administered orally occurs within 30 minutes and is maximal at approximately 2 1/2 hours. The pharmacological mode of action of acetaminophen is unknown at this time.

Acetaminophen is rapidly and almost completely absorbed from the gastrointestinal tract. In 24 normal volunteers the time to mean peak plasma concentration was 1 hour (range 0.25 to 3 hours) after oral administration and the mean plasma elimination half-life was 2.8 hours (range 2 to 4 hours).

The effect of pentazocine on acetaminophen plasma protein binding or vice versa has not been established. For acetaminophen there is little or no plasma protein binding at normal therapeutic doses. When toxic doses of acetaminophen are ingested and drug plasma levels exceed 90 mcg/mL, plasma binding may vary from 8% to 43%.

Acetaminophen is conjugated in the liver with glucuronic acid and to a lesser extent with sulfuric acid. Approximately 80% of acetaminophen is excreted in the urine after conjugation and about 3% is excreted unchanged. The drug is also conjugated to a lesser extent with cysteine and additionally metabolized by hydroxylation.

If pentazocine hydrochloride and acetaminophen tablets are taken every 4 hours over an extended period of time, accumulation of pentazocine and to a lesser extent, acetaminophen, may occur.

INDICATIONS AND USAGE

Pentazocine Hydrochloride and Acetaminophen Tablets are indicated for the relief of mild to moderate pain.

CONTRAINDICATIONS

Pentazocine hydrochloride and acetaminophen tablets are contraindicated in patients who are hypersensitive to either pentazocine or acetaminophen.

WARNINGS

Hepatotoxicity

Pentazocine hydrochloride and acetaminophen tablets contain acetaminophen and pentazocine hydrochloride. Acetaminophen has been associated with cases of acute liver failure, at times resulting in liver transplant and death. Most of the cases of liver injury are associated with the use of acetaminophen at doses that exceed 4000 milligrams per day, often involve more than one acetaminophen-containing product. The excessive intake of acetaminophen may be intentional to cause self-harm or unintentional as patients attempt to obtain more pain relief or unknowingly take other acetaminophen-containing products.

The risk of acute liver failure is higher in individuals with underlying liver disease and in individuals who ingest alcohol while taking acetaminophen.

Instruct patients to look for acetaminophen or APAP on package labels and not to use more than one product that contains acetaminophen. Instruct patients to seek medical attention immediately upon ingestion of more than 4000 milligrams of acetaminophen per day, even if they feel well.

Hypersensitivity/anaphylaxis

There have been post-marketing reports of hypersensitivity and anaphylaxis associated with use of acetaminophen. Clinical signs included swelling of the face, mouth, and throat, respiratory distress, urticaria, rash, pruritus, and vomiting. There were infrequent reports of life-threatening anaphylaxis requiring emergent medical attention. Instruct patients to discontinue pentazocine hydrochloride and acetaminophen tablets immediately and seek medical care if they experience these symptoms. Do not prescribe pentazocine hydrochloride and acetaminophen tablets for patients with acetaminophen allergy.

Drug Dependence

Pentazocine can cause a physical and psychological dependence. (See DRUG ABUSE AND DEPENDENCE.)

Use In Head Injury and Increased Intracranial Pressure

In the presence of head injury, intracranial lesions or a preexisting increase in intracranial pressure, the possible respiratory depressant effects of pentazocine and its potential to elevate cerebrospinal fluid pressure (resulting from vasodilation following CO2 retention) may be markedly increased. Furthermore, pentazocine can produce effects on pupillary response and consciousness, which may obscure neurologic signs of further increases in intracranial pressure in patients with head injuries. In such patients, pentazocine hydrochloride and acetaminophen tablets must be used with extreme caution and only if its use is deemed essential.

Interactions with Alcohol and Drugs of Abuse

Pentazocine may be expected to have additive effects when used in conjunction with alcohol, other opioids, or illicit drugs that cause central nervous system depression because respiratory depression, hypotension, profound sedation, coma or death may result.

Patients Receiving Narcotics

Pentazocine is a mild narcotic antagonist. Some patients previously given narcotics, including methadone for the daily treatment of narcotic dependence, have experienced withdrawal symptoms after receiving pentazocine.

Respiratory Depression

Respiratory depression occurs more frequently in elderly or debilitated patients and in those suffering from conditions accompanied by hypoxia, hypercapnia, or upper airway obstruction, in whom even moderate therapeutic doses may significantly decrease pulmonary ventilation. Use pentazocine hydrochloride and acetaminophen tablets with extreme caution in patients with chronic obstructive pulmonary disease or cor pulmonale and in patients having a substantially decreased respiratory reserve (e.g., severe kyphoscoliosis), hypoxia, hypercapnia, or pre-existing respiratory depression. Alternative non-opioid analgesics should be considered, and pentazocine hydrochloride and acetaminophen tablets should be employed only under careful medical supervision at the lowest effective dose in such patients.

Acute CNS Manifestations

Patients receiving therapeutic doses of pentazocine hydrochloride and acetaminophen tablets have experienced hallucinations (usually visual), disorientation, and confusion which have cleared spontaneously within a period of hours. The mechanism of this reaction is not known. Such patients should be closely observed and vital signs checked. If the drug is reinstituted, it should be done with caution since these acute CNS manifestations may recur.

PRECAUTIONS

Drug Abuse and Dependence

Pentazocine hydrochloride and acetaminophen tablets are a Schedule IV controlled substance.

Abuse and addiction are separate and distinct from physical dependence and tolerance. Abuse is characterized by misuse of a drug for non-medical purposes, often in combination with other psychoactive substances. Addiction is a disease of repeated drug abuse. Addiction is a primary, chronic, neurobiologic disease, with genetic, psychosocial, and environmental factors influencing its development and manifestations. Addiction is characterized by behaviors that include one or more of the following: impaired control over drug use, compulsive use, continued use despite harm, and craving. Drug addiction is a treatable disease, utilizing a multidisciplinary approach, but relapse is common. Physical dependence is a state of adaptation that is manifested by a specific withdrawal syndrome that can be produced by abrupt cessation, rapid dose reduction, decreasing blood level of the drug, and/or administration of an antagonist. Tolerance is a state of adaptation in which exposure to a drug induces changes that result in a diminution of one or more of the drug’s effects over time. Tolerance may occur to both the desired and undesired effects of drugs, and may develop at different rates for different effects.

Physicians should be aware that addiction may not be accompanied by concurrent tolerance and symptoms of physical dependence in all addicts. In addition, abuse of opioids can occur in the absence of addiction and is characterized by misuse of the drug for non-medical purposes, and often in combination with other psychoactive substances.

There have been some reports of dependence and of withdrawal symptoms with pentazocine hydrochloride and acetaminophen tablets. Patients with a history of drug dependence should be under close supervision while receiving pentazocine orally. There have been rare reports of possible abstinence syndromes in newborns after prolonged use of pentazocine during pregnancy.

There have been reports of development of addiction and physical dependence in patients receiving parenteral pentazocine. People with a history of drug abuse or alcohol abuse may have a higher chance of becoming addicted to opioid medicines.

Abrupt dose cessation or rapid dose reduction following the extended use of parenteral pentazocine has resulted in withdrawal symptoms such as abdominal cramps, nausea, vomiting, elevated temperature, chills, rhinorrhea, restlessness, anxiety, or lacrimation. In general opioid therapy should not be abruptly discontinued. When the patient no longer requires treatment with pentazocine hydrochloride and acetaminophen tablets, the drug should be tapered gradually to prevent signs and symptoms of withdrawal in patients who have been receiving opioids for an extended period of time and might have become physically dependent.

In prescribing pentazocine hydrochloride and acetaminophen tablets for chronic use, the physician should take under consideration that proper assessment of the patient, proper prescribing practices, periodic re-evaluation of therapy, and proper dispensing and storage are appropriate measures that help to identify and decrease misuse and abuse of opioid drugs.

Severe, even lethal, consequences may result from misuse of tablets by injection either alone or in combination with other substances, such as pulmonary emboli, vascular occlusion, ulceration and abscesses, and withdrawal symptoms in narcotic dependent individuals.

CNS Effect

Caution should be used when pentazocine hydrochloride and acetaminophen tablets are administered to patients prone to seizures; seizures have occurred in a few such patients in association with the use of pentazocine although no cause and effect relationship has been established.

Porphyria

Particular caution should be exercised in administering pentazocine to patients with porphyria since it may provoke an acute attack in susceptible individuals.

Cardiovascular Disease

Pentazocine can elevate blood pressure, possibly through the release of endogenous catecholamines. Particular caution should be exercised in conditions where alterations in vascular resistance and blood pressure might be particularly undesirable, such as in the acute phase of myocardial infarction.

Pentazocine hydrochloride and acetaminophen tablets should be used with caution in patients with myocardial infarction who have nausea or vomiting.

Impaired Renal or Hepatic Function

Decreased metabolism of the drug by the liver in extensive liver disease may predispose to accentuation of side effects. Although laboratory tests have not indicated that pentazocine causes or increases renal or hepatic impairment, the drug should be administered with caution to patients with such impairment.

Acetaminophen is metabolized by the liver, and has been associated with cases of acute liver failure, at times resulting in liver transplant and death. Therefore, pentazocine hydrochloride and acetaminophen tablets should be administered with caution to patients with hepatic impairment and in individuals who ingest alcohol (See BOXED WARNING and WARNINGS, Hepatotoxicity).

Other

Caution should also be observed when administering pentazocine hydrochloride and acetaminophen tablets in patients with hypothyroidism, adrenocortical insufficiency, prostate hypertrophy, inflammatory or obstructive bowel disease, acute abdominal syndromes of unknown etiology, cholecystitis, pancreatitis, or acute alcohol intoxication and delirium tremens.

Biliary Surgery

Narcotic drug products are generally considered to elevate biliary tract pressure for varying periods following their administration. Some evidence suggests that pentazocine may differ from other marketed narcotics in this respect (i.e., it causes little or no elevation in biliary tract pressures). The clinical significance of these findings, however, is not yet known.

Information for Patients

Patients receiving pentazocine hydrochloride and acetaminophen tablets should be given the following instructions by the physician:

- Do not take pentazocine hydrochloride and acetaminophen tablets if you are allergic to any of its ingredients.
- If you develop signs/symptoms of allergy such as a rash, hives, itching, vomiting, swelling of the face or mouth, or difficulty breathing, stop taking pentazocine hydrochloride and acetaminophen tablets and contact your healthcare provider immediately.
- Do not take more than 4000 milligrams of acetaminophen (alone or in combination with other products containing acetaminophen). Seek medical attention immediately upon ingestion of more than 4000 milligrams of acetaminophen per day, even if you feel well. Look for acetaminophen or APAP on package labels. Do not use more than one product that contains acetaminophen.
- Contact your healthcare provider if you took more than the recommended dose.
- Patients should be advised that pentazocine hydrochloride and acetaminophen tablet is a narcotic pain reliever, and should be taken only as directed.
- The dose of pentazocine hydrochloride and acetaminophen tablets should not be adjusted without consulting with a physician or other healthcare professional.
- Patients should be advised that pentazocine hydrochloride and acetaminophen tablets may cause drowsiness, dizziness, or lightheadedness and may impair mental and/or physical ability required for the performance of potentially hazardous tasks (e.g., driving, operating machinery). Patients started on pentazocine hydrochloride and acetaminophen tablets or patients whose dose has been adjusted should refrain from any potentially dangerous activity until it is established that they are not adversely affected.
- Pentazocine hydrochloride and acetaminophen tablets will add to the effect of alcohol and other CNS depressants (such as antihistamines, sedatives, hypnotics, tranquilizers, general anesthetics, phenothiazines, other opioids, and monoamine oxidase [MAO]inhibitors).
- Patients should not combine pentazocine hydrochloride and acetaminophen tablets with alcohol or other central nervous system depressants (sleep aids, tranquilizers) except by the orders of the prescribing physician, because dangerous additive effects may occur, resulting in serious injury or death.
- Women of childbearing potential who become or are planning to become pregnant should consult a physician prior to initiating or continuing therapy with pentazocine hydrochloride and acetaminophen tablets.
- Safe use in pregnancy has not been established. Prolonged use of opioid analgesics during pregnancy may cause neonatal physical dependence, and neonatal withdrawal may occur.
- If patients have been receiving treatment with pentazocine hydrochloride and acetaminophen tablets for more than a few weeks and cessation of therapy is indicated, they should be counseled on the importance of safely tapering the dose and that abruptly discontinuing the medication could precipitate withdrawal symptoms. The physician should provide a dose schedule to accomplish a gradual discontinuation of the medication.
- Patients should be advised that pentazocine hydrochloride and acetaminophen tablets are a potential drug of abuse. They should protect it from theft. It should never be given to anyone other than the individual for whom it was prescribed.
- Patients should be instructed to keep pentazocine hydrochloride and acetaminophen tablets in a secure place out of the reach of children. When pentazocine hydrochloride and acetaminophen tablets are no longer needed, please consult your pharmacist for proper disposal instructions.
- As with other opioids, patients taking pentazocine hydrochloride and acetaminophen tablets should be advised of the potential for severe constipation; appropriate laxatives and/or stool softeners as well as other appropriate treatments should be initiated from the onset of opioid therapy.
- Patients should be advised of the most common adverse events that may occur while taking pentazocine hydrochloride and acetaminophen tablets: constipation, nausea, somnolence, lightheadedness, dizziness, sedation, vomiting, and sweating.

Drug Interactions

CNS Depressants

Other central nervous system (CNS) depressants including sedatives, hypnotics, general anesthetics, antiemetics, phenothiazines, or other tranquilizers or alcohol increases the risk of respiratory depression, hypotension, profound sedation, or coma. Use morphine sulfate with caution and in reduced dosages in patients taking these agents.

Opioid Agonist Analgesics

Pentazocine hydrochloride and acetaminophen tablets can antagonize the effects of a pure opioid agonist analgesic and/or may precipitate withdrawal symptoms.

Monoamine Oxidase Inhibitors (MAOIs)

Concomitant use of monoamine oxidase inhibitors (MAOIs) with pentazocine hydrochloride and acetaminophen tablets may cause CNS excitation and hypertension through their respective effects on catecholamines. Caution should therefore be observed in administering pentazocine hydrochloride and acetaminophen tablets to patients who are currently receiving MAOIs or who have received them within the preceding 14 days.

Anticholinergics

Anticholinergics or other medications with anticholinergic activity when used concurrently with opioid analgesics may result in increased risk of urinary retention and/or severe constipation, which may lead to paralytic ileus.

Tobacco

Smoking tobacco could enhance the metabolic clearance rate of pentazocine reducing the clinical effectiveness of a standard dose of pentazocine.

Carcinogenesis, Mutagenesis, Impairment of Fertility

Carcinogenesis, mutagenesis, and impairment of fertility studies have not been done with this combination product.

Studies to evaluate the mutagenic potential of the components of pentazocine hydrochloride and acetaminophen tablets have not been conducted.

Pentazocine, when administered orally or parenterally, had no adverse effect on either the reproductive capabilities or the course of pregnancy in rabbits and rats. Embryotoxic effects on the fetuses were not shown.

The daily administration of 4 mg/kg to 20 mg/kg pentazocine subcutaneously to female rats during a 14 day pre-mating period and until the 13th day of pregnancy did not have any adverse effects on the fertility rate.

Pregnancy

Teratogenic Effects

Pregnancy Category C

There are no adequate and well-controlled studies in pregnant women. Pentazocine hydrochloride and acetaminophen tablets should be used during pregnancy only if the potential benefit justifies the potential risk to the fetus.

Animal studies with the combination of pentazocine and acetaminophen have not been completed.

In a published report, a single dose of pentazocine administered to pregnant hamsters on gestation day 8 increased the incidence of exencephaly and cranioschisis at a dose of 196 mg/kg, SC (0.2-times the maximum daily human dose of pentazocine via 6 caplets on a mg/m^2 basis).

Nonteratogenic Effects

There has been no experience in this regard with the combination pentazocine and acetaminophen. However, there have been rare reports of possible abstinence syndromes in newborns after prolonged use of pentazocine during pregnancy. Frequent use of acetaminophen (defined as most days or daily use) in late pregnancy may be associated with an increased risk of persistent wheezing in the infant which may persist into childhood.

Labor and Delivery

Patients receiving pentazocine during labor have experienced no adverse effects other than those that occur with commonly used analgesics. However, pentazocine can cross the placental barrier and cause central nervous system depression in the newborn and, if used regularly throughout pregnancy, may lead to symptoms of withdrawal in the newborn. Pentazocine hydrochloride and acetaminophen tablets should be used with caution in women delivering premature infants. The effect of pentazocine hydrochloride and acetaminophen tablets on the mother and fetus, the duration of labor or delivery, the possibility that forceps delivery or other intervention or resuscitation of the newborn may be necessary, or the effect of pentazocine hydrochloride and acetaminophen tablets, on the later growth, development, and functional maturation of the child are unknown at the present time.

Nursing Mothers

Pentazocine and acetaminophen are excreted in human milk. Caution should be exercised when pentazocine hydrochloride and acetaminophen tablets are administered to a nursing woman.

Pediatric Use

Safety and effectiveness in pediatric patients below the age of 12 have not been established.

Geriatric Use

Clinical studies of pentazocine hydrochloride and acetaminophen tablets did not include sufficient numbers of subjects aged 65 and over to determine whether they respond differently from younger subjects. Other reported clinical experience has not identified differences in responses between the elderly and younger patients. In general, dose selection for an elderly patient should be cautious, usually starting at the low end of the dosing range, reflecting the greater frequency of decreased hepatic, renal, or cardiac function, and of concomitant disease or other drug therapy.

ADVERSE REACTIONS

Clinical experience with pentazocine hydrochloride and acetaminophen tablets have been insufficient to define all possible adverse reactions with this combination. However, reactions reported after oral administration of pentazocine hydrochloride in 50 mg dosage include the following:

Cardiovascular: hypertension, hypotension, circulatory depression, tachycardia.

Respiratory: rarely respiratory depression,

Acute CNS Manifestations: Hallucinations (usually visual), disorientation, and confusion

Other CNS effects: grand mal convulsions, increase in intracranial pressure, dizziness, lightheadedness, hallucinations, sedation, euphoria, headache, confusion, disorientation; infrequently weakness, disturbed dreams, insomnia, syncope, and depression; and rarely tremor, irritability, excitement, tinnitus.

Autonomic: sweating; infrequently flushing; and rarely chills.

Gastrointestinal: nausea, vomiting, constipation; diarrhea, anorexia, dry mouth, Biliary tract spasm, and rarely abdominal distress.

Allergic: edema of the face, anaphylactic shock, dermatitis including pruritus, flushed skin including plethora, infrequently rash; and rarely urticaria.

Ophthalmic: visual blurring and focusing difficulty, miosis.

Hematologic: depression of white blood cells (especially granulocytes) with rare cases of agranulocytosis, which is usually reversible, moderate transient eosinophilia.

Dependence and Withdrawal Symptoms: (See WARNINGS, PRECAUTIONS, and DRUG ABUSE AND DEPENDENCE Sections).

Other: urinary retention, paresthesia, serious skin reactions, including erythema multiforme, Stevens-Johnson Syndrome, toxic epidermal necrolysis, and alterations in rate or strength of uterine contractions during labor.

A few cases of hypersensitivity to acetaminophen have been reported, as manifested by anaphylaxis, angioneurotic edema, thrombocytopenic purpura, skin rashes, and rarely hemolytic anemia and agranulocytosis. Occasionally individuals respond to ordinary doses with nausea and vomiting and diarrhea.

OVERDOSAGE

Signs and Symptoms

For pentazocine alone in single doses above 60 mg there have been reports of the occurrence of nalorphine-like psychotomimetic effects such as anxiety, nightmares, strange thoughts, and hallucinations. Somnolence, marked respiratory depression associated with increased blood pressure and tachycardia have also resulted as have seizures, hypotension, dizziness, nausea, vomiting, lethargy, and paresthesias. The respiratory depression is antagonized by naloxone (see Treatment). Circulatory failure and deepening coma may occur in more severe cases, particularly in patients who have also ingested other CNS depressants such as alcohol, sedative/hypnotics, or antihistamines.

In acetaminophen overdosage: dose-dependent, potentially fatal hepatic necrosis is the most serious adverse effect. Renal tubular necrosis, hypoglycemic coma, and coagulation defects may also occur. Early symptoms following a potentially hepatotoxic overdose may include: nausea, vomiting, diaphoresis, and general malaise. Clinical and laboratory evidence of hepatic toxicity may not be apparent until 48-72 hours post-ingestion.

Treatment

Adequate measures to maintain ventilation and general circulatory support should be employed. Assisted or controlled ventilation, intravenous fluids, vasopressors, and other supportive measures should be employed as indicated. Consideration should be given to gastric lavage and gastric aspiration to reduce drug absorption.

Oxygen, intravenous fluids, vasopressors, and other supportive measures should be employed as indicated. Assisted or controlled ventilation should also be considered. For respiratory depression due to overdosage or unusual sensitivity to pentazocine hydrochloride and acetaminophen tablets, parenteral naloxone is a specific and effective antagonist.

Gastric decontamination with activated charcoal should be administered just prior to N-acetylcysteine (NAC) to decrease systemic absorption if acetaminophen ingestion is known or suspected to have occurred within a few hours of presentation. Serum acetaminophen levels should be obtained immediately if the patient presents 4 hours or more after ingestion to assess potential risk of hepatotoxicity; acetaminophen levels drawn less then 4 hours post-ingestion may be misleading. To obtain the best possible outcome, NAC should be administered as soon as possible where impending or evolving liver injury is suspected. Intravenous NAC may be administered when circumstances preclude oral administration.

Vigorous supportive therapy is required in severe intoxication. Procedures to limit the continuing absorption of the drug must be readily performed since the hepatic injury is dose dependent and occurs early in the course of intoxication.

DOSAGE AND ADMINISTRATION

Adult

The usual adult dose is 1 caplet every 4 hours as needed for pain relief, up to a maximum of 6 caplets per day.

Discontinuation

Due to the potential for withdrawal symptoms associated with abrupt discontinuation, consideration should be given to tapering patients off pentazocine hydrochloride and acetaminophen tablets after prolonged periods of treatment with pentazocine hydrochloride and acetaminophen tablets (See PRECAUTIONS, Drug Abuse and Dependence).

HOW SUPPLIED

Pentazocine Hydrochloride and Acetaminophen Tablets are light blue capsule shaped, tablets debossed “NL” on left side and “670” on right side of bisect and plain on the other side.

Bottles of 100 (NDC 43386-670-01).

Bottles of 100 (NDC 43386-670-05)

Store at 25°C (77°F); excursions permitted between 15°-30°C (59°-86°F). [See USP.]

Dispense in a tight, light-resistant container as defined in the USP.

DEA Order Form Required.

Manufactured by:
Novel Laboratories, Inc.
Somerset, NJ 08873

Distributed by:
GAVIS Pharmaceuticals, LLC
Somerset, NJ 08873

GIN-670-02
Rev: 06/2011